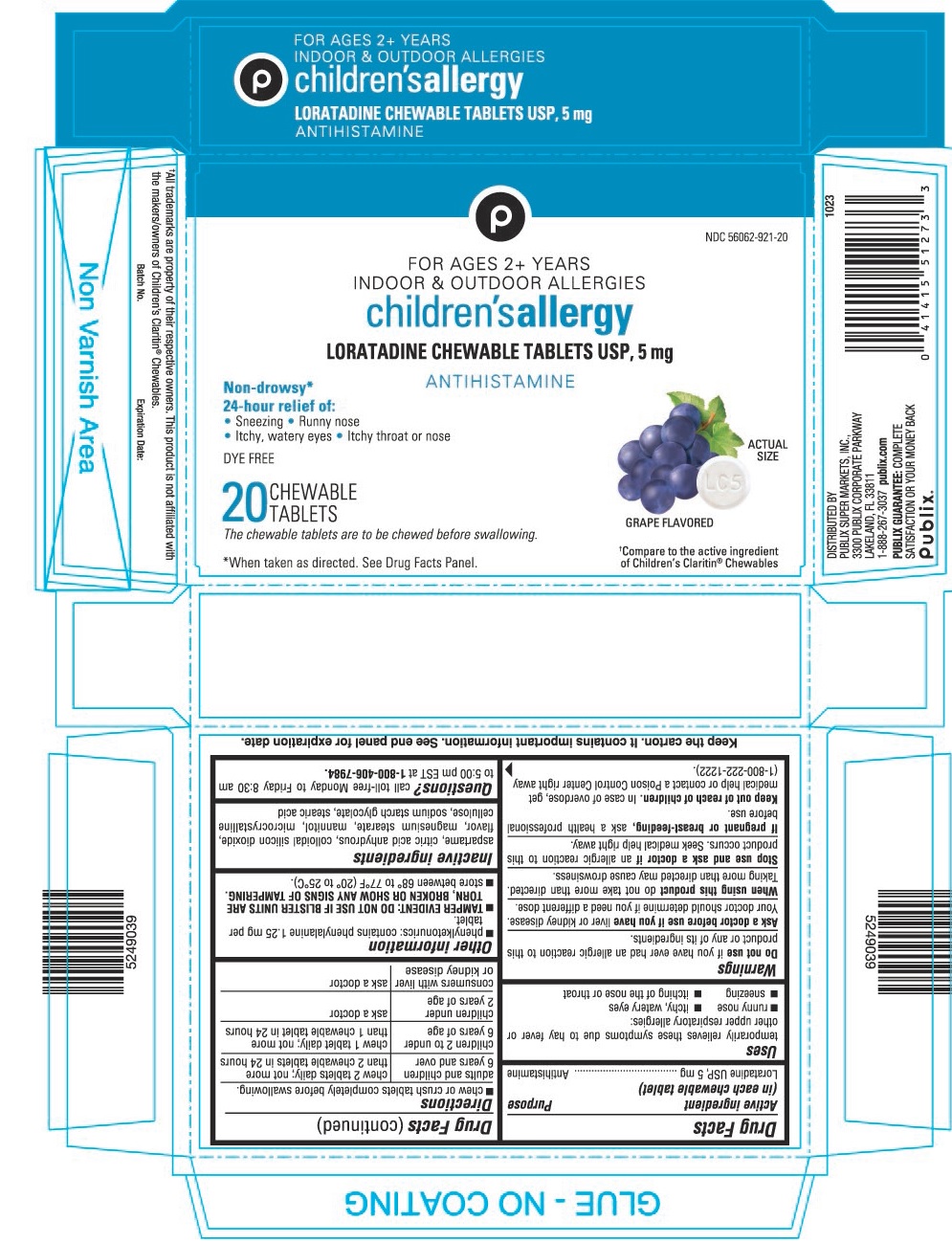 DRUG LABEL: DYE-FREE CHILDRENS LORATADINE
NDC: 56062-921 | Form: TABLET, CHEWABLE
Manufacturer: PUBLIX SUPER MARKETS, INC
Category: otc | Type: HUMAN OTC DRUG LABEL
Date: 20240315

ACTIVE INGREDIENTS: LORATADINE 5 mg/1 1
INACTIVE INGREDIENTS: ASPARTAME; ANHYDROUS CITRIC ACID; SILICON DIOXIDE; MAGNESIUM STEARATE; MANNITOL; MICROCRYSTALLINE CELLULOSE; SODIUM STARCH GLYCOLATE TYPE A POTATO; STEARIC ACID

Dye-Free Children's Loratadine Chewable Tablets USP, 5 mg

Drug Facts

Active ingredient (in each chewable tablet)

Loratadine USP, 5 mg

Purpose

Antihistamine

Uses

temporarily relieves these symptoms due to hay fever or other upper respiratory allergies:

- runny nose
- itchy, watery eyes
- sneezing
- itching of the nose or throat

Warnings

DO NOT USE

Do not useif you have ever had an allergic reaction to this product or any of its ingredients.

Ask a doctor before use if you haveliver or kidney disease. Your doctor should determine if you need a different dose.

WHEN USING

When using this productdo not take more than directed. Taking more than directed may cause drowsiness.

Stop use and ask a doctor ifan allergic reaction to this product occurs. Seek medical help right away.

PREGNANCY OR BREAST FEEDING

If pregnant or breast-feeding,ask a health professional before use.

Keep out of reach of children.In case of overdose, get medical help or contact a Poison Control Center right away (1-800-222-1222).

Directions

- chew or crush tablets completely before swallowing.

adults and children 6 years and over | chew 2 tablets daily; not more than 2 chewable tablets in 24 hours
children 2 to under 6 years of age | chew 1 tablet daily; not more than 1 chewable tablet in 24 hours
children under 2 years of age | ask a doctor
consumers with liver or kidney disease | ask a doctor

Other information

- phenylketonurics: contains phenylalanine 1.25 mg per tablet.
- TAMPER EVIDENT: DO NOT USE IF BLISTER UNITS ARE TORN, BROKEN OR SHOW ANY SIGNS OF TAMPERING.
- store between 68° to 77°F (20° to 25°C).

Inactive ingredients

aspartame, citric acid anhydrous, colloidal silicon dioxide, flavor, magnesium stearate, mannitol, microcrystalline cellulose, sodium starch glycolate, stearic acid

DISTRIBUTED BY
PUBLIX SUPER MARKETS, INC.,
3300 PUBLIX CORPORATE PARKWAY
LAKELAND, FL 33811

PRINCIPAL DISPLAY PANEL - 5 mg Tablet Blister Pack Carton

NDC 56062-921-20

FOR AGES 2+ YEARS
INDOOR & OUTDOOR ALLERGIES

children'sallergy

LORATADINE CHEWABLE TABLETS USP, 5 mg

ANTIHISTAMINE

Non-drowsy*
24-hour relief of:
• Sneezing • Runny nose
• Itchy, watery eyes • Itchy throat or nose

DYE FREE

ACTUAL
SIZE

20
CHEWABLE
TABLETS

GRAPE FLAVORED

*When taken as directed. See Drug Facts Panel

†Compare to the active ingredient
of Children's Claritin®Chewables